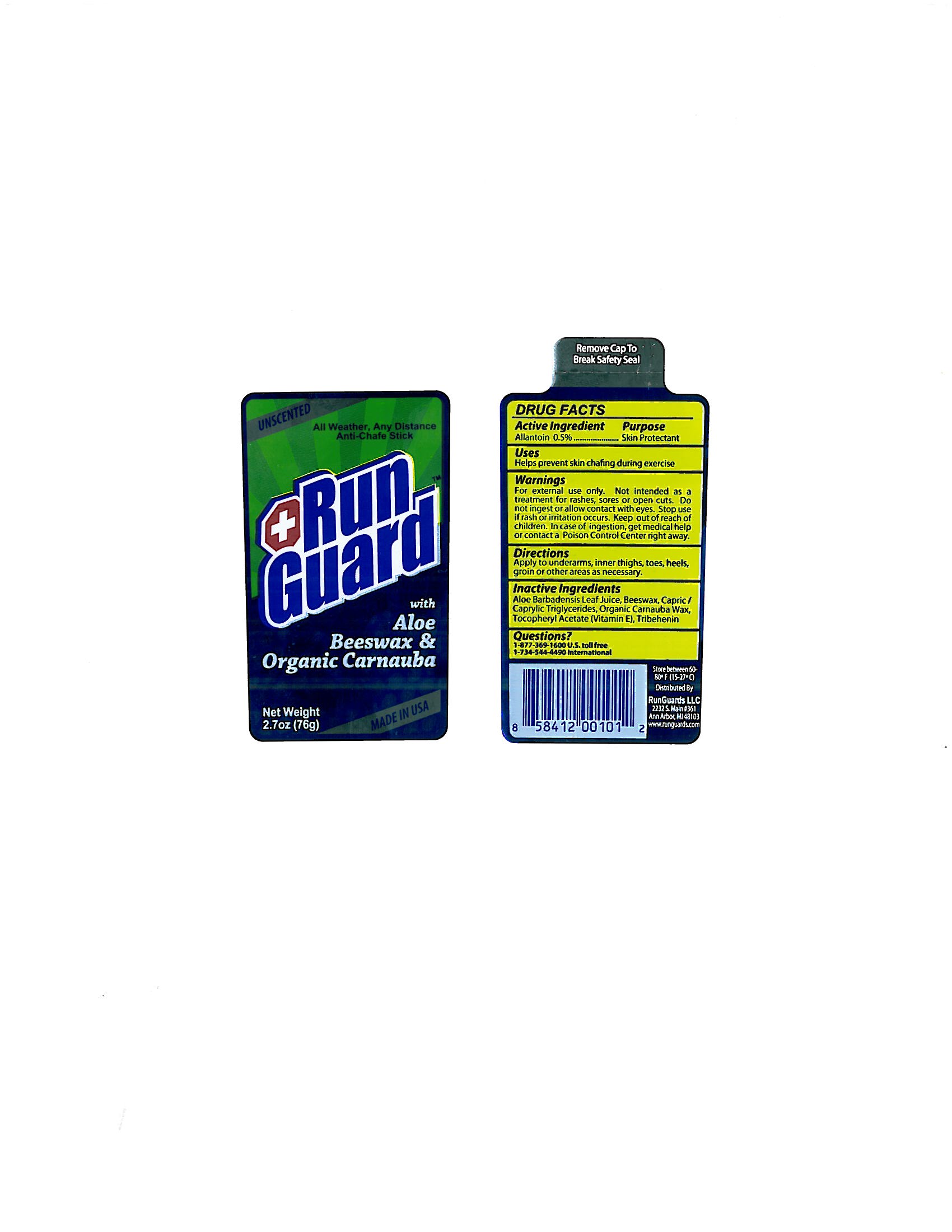 DRUG LABEL: Run Guard Original
NDC: 24474-001 | Form: STICK
Manufacturer: RunGuards LLC
Category: otc | Type: HUMAN OTC DRUG LABEL
Date: 20140826

ACTIVE INGREDIENTS: ALLANTOIN 0.5 g/100 g
INACTIVE INGREDIENTS: ALOE VERA LEAF; YELLOW WAX; MEDIUM-CHAIN TRIGLYCERIDES; CARNAUBA WAX; .ALPHA.-TOCOPHEROL ACETATE; TRIBEHENIN

Drug Facts

Active Ingredient

Allantoin 0.5%

Purpose

Skin Protectant

Uses

Helps prevent skin chafing during exercise

Warnings

For external use only.

Not intended as a treatment for rashes, sores or open cuts. Do not ingest or allow contact with eyes. Stop use if rash or irritation occurs.

Keep out of reach of children.

In case of ingestion, get medical help or contact a Poison Control Center right away.

Directions

Apply to underarms, inner thighs, toes, heels, groin or other areas as necessary.

Inactive Ingredients

Aloe Barbadensis Leaf Juice, Beeswax, Capric/Caprylic Triglycerides, Organic Carnauba Wax, Tocopheryl Acetate (Vitamin E), Tribehenin

Questions?

1-877-369-1600 U.S. toll free

1-734-544-4490 International

PACKAGE LABEL

UNSCENTED

All Weather, Any Distance

Anti-Chafe Stick

+Run

Guard

with

Aloe

Beeswax and

Organic Carnauba

Net Weight

2.7 oz (76g)

MADE IN USA